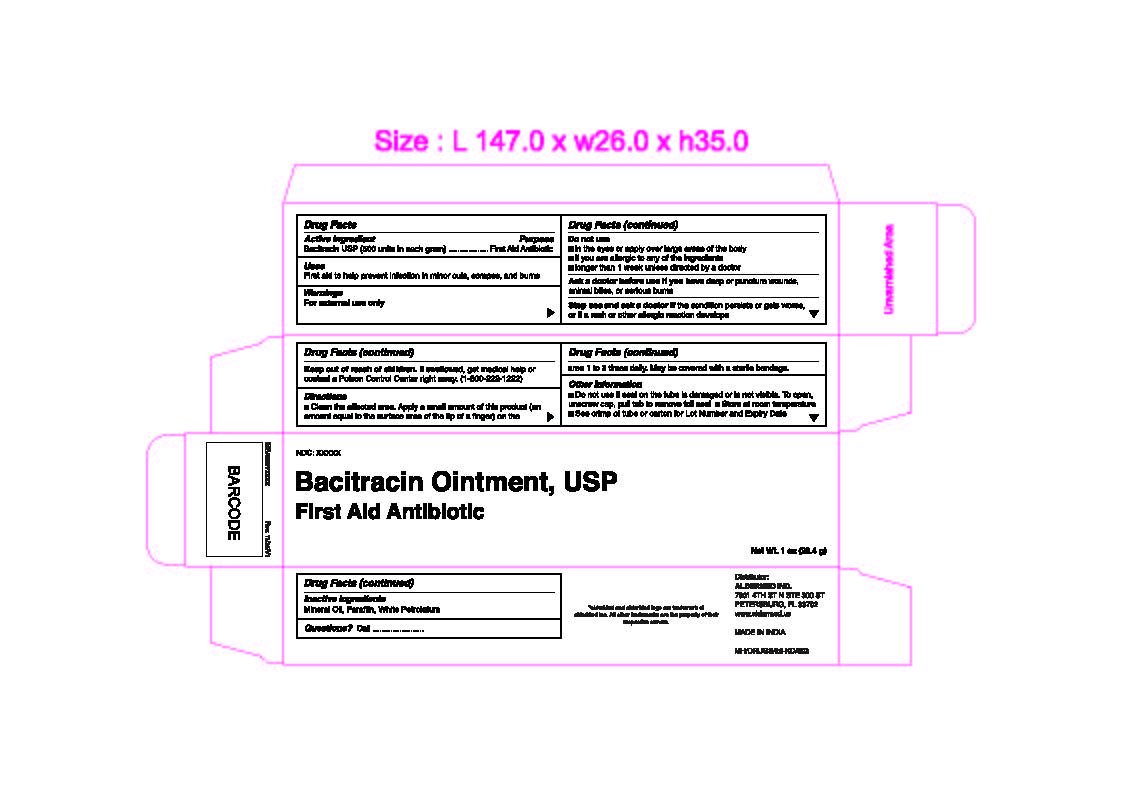 DRUG LABEL: Bacitracin
NDC: 87236-000 | Form: OINTMENT
Manufacturer: AlderMed Inc.
Category: otc | Type: HUMAN OTC DRUG LABEL
Date: 20260212

ACTIVE INGREDIENTS: BACITRACIN 500 [iU]/1 g
INACTIVE INGREDIENTS: MINERAL OIL; PARAFFIN; WHITE PETROLATUM

Bacitracin Ointment

Active ingredient

Bacitracin USP (500 Units in each gram)

Purpose

First Aid Antibiotic

Uses

- First aid to help prevent infection in minor cuts, scrapes and burns

Warnings

For external use only

Do not use

- in the eyes or apply over large areas of body
- if you are allergic to any of the ingredients
- longer than 1 week unless directed by a doctor

Ask a doctor before use if you have

deep or puncture wounds, animal bites, or serious burns

Stop use and ask a doctor if

the condition persists or gets worse, or if a rash or other allergic reaction develops.

Keep out of reach of children

If swallowed, get medical help or contact a Poison Control Centre right away (1-800-222-1222)

Directions

Clean the affected area. Apply a small amount of this product (an amount equal to the surface area of the tip of a finger) on the area 1 to 3 times daily. May be covered with a sterile bandage.

Other information

- Do not use if seal on the tube is damaged or is not visible. To open, unscrew cap, pull tab to remove foil seal
- Store at room temperature
- See crimp of tube or carton for Lot Number and Expiry Date

Inactive Ingredients

Mineral Oil, Paraffin, White Petrolatum

Questions?

Call 1-833-605-84-74 9am-5 pm EST M-F